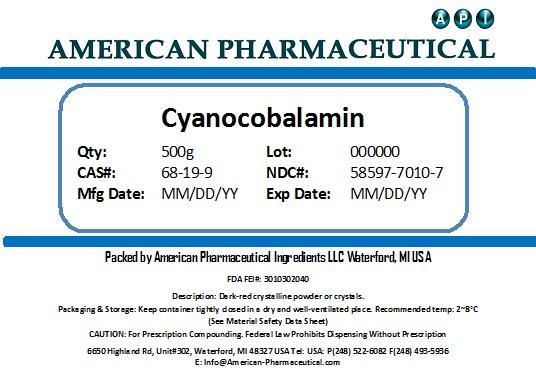 DRUG LABEL: Cyanocobalamin
NDC: 58597-7010 | Form: POWDER
Manufacturer: AMERICAN PHARMACEUTICAL INGREDIENTS LLC
Category: other | Type: BULK INGREDIENT
Date: 20131101

ACTIVE INGREDIENTS: Cyanocobalamin 1 g/1 g

Cyanocobalamin